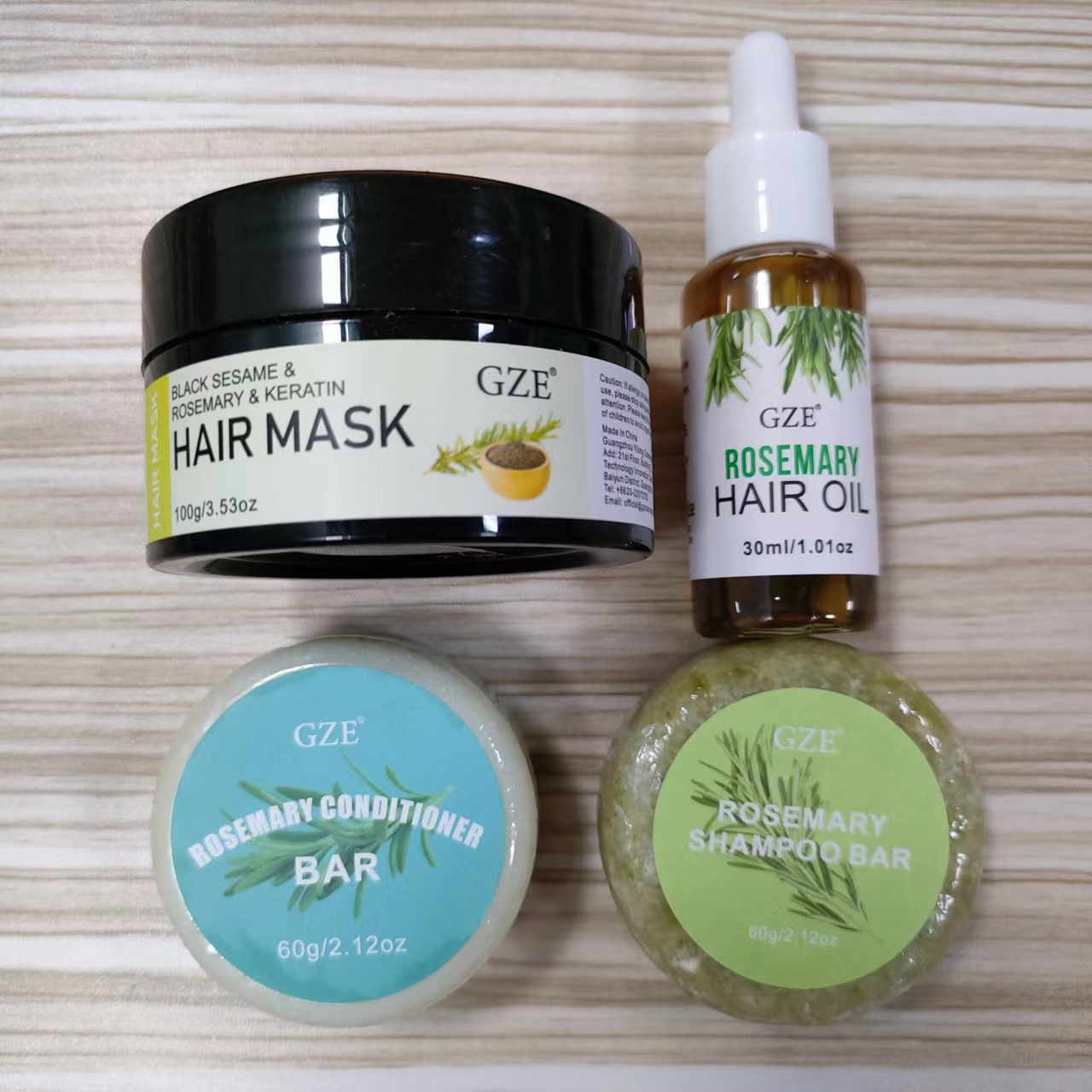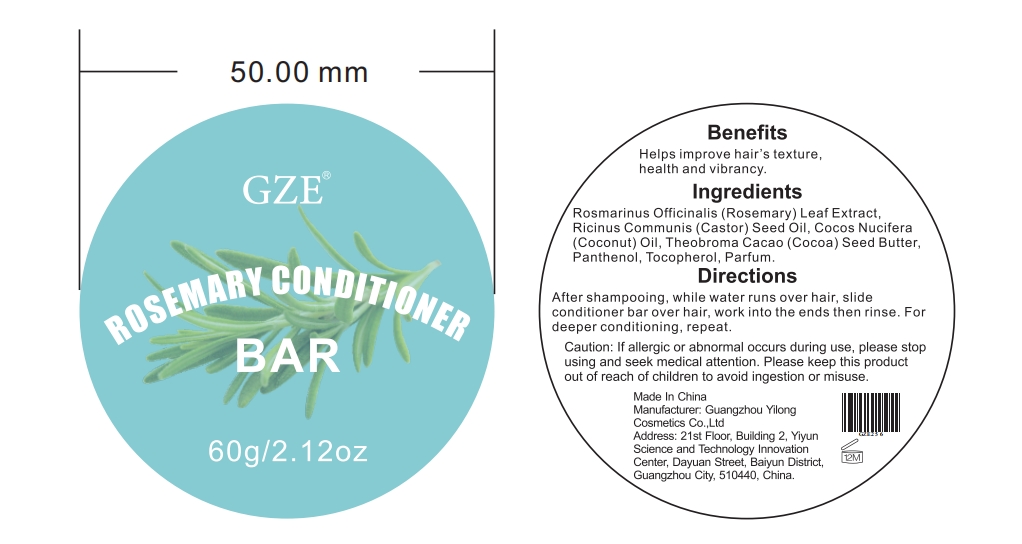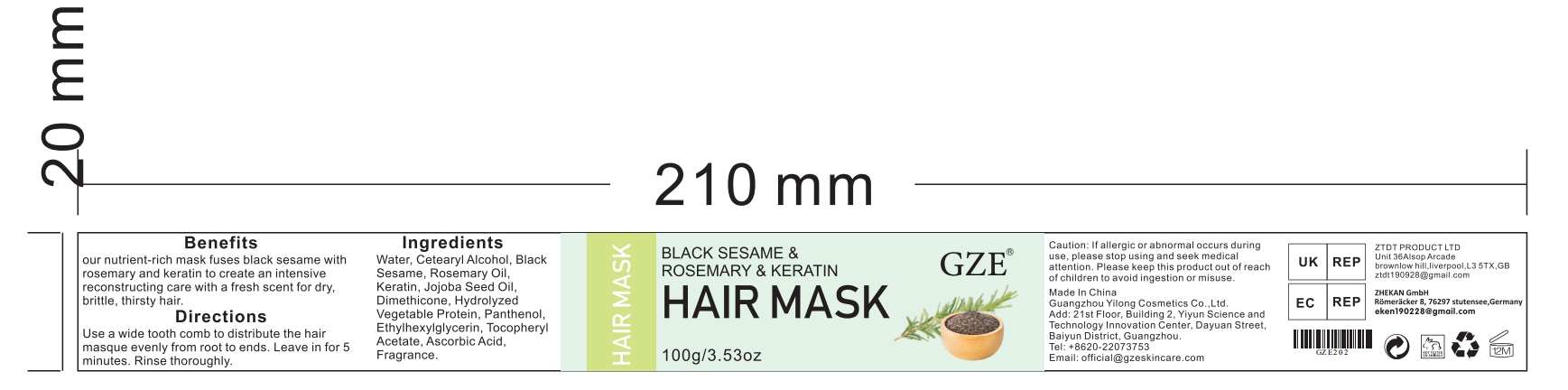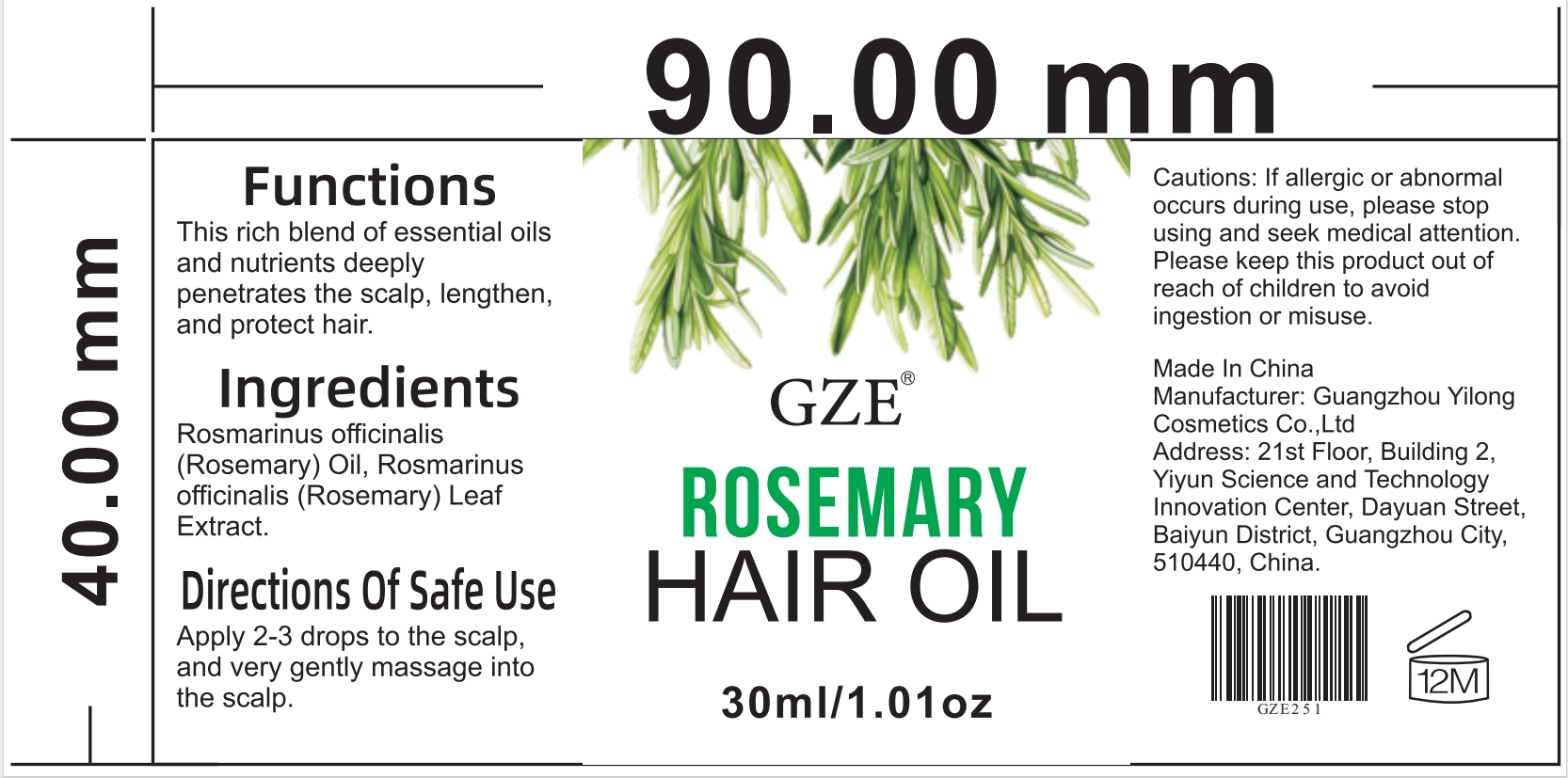 DRUG LABEL: GZE Rosemary Hair CareSet
NDC: 83566-016 | Form: KIT | Route: TOPICAL
Manufacturer: Guangzhou Yilong Cosmetics Co., Ltd
Category: otc | Type: HUMAN OTC DRUG LABEL
Date: 20240628

ACTIVE INGREDIENTS: ROSEMARY OIL 46 g/100 mL; ROSEMARY OIL 46 g/100 g; ROSEMARY OIL 5 g/100 g; ROSEMARY OIL 5 g/100 g
INACTIVE INGREDIENTS: ASCORBYL PALMITATE; CYCLOMETHICONE 4; HYDROLYZED JOJOBA ESTERS (ACID FORM); ASCORBIC ACID; MENTHA PIPERITA LEAF; RETINYL RETINOATE; TOCOPHEROL; WATER; PANTHENOL; COCONUT OIL; COCOA BUTTER; PANTHENOL; PARFUMIDINE; TOCOPHEROL; RICINUS COMMUNIS SEED; ETHYLHEXYLGLYCERIN; ASCORBYL TOCOPHERYL MALEATE; FRAGRANCE 13576; ASCORBIC ACID; PANTHENOL; CETEARYL BEHENATE; SESAME SEED; CETYL DIMETHICONE 150; HYDROLYZED JOJOBA ESTERS (ACID FORM); HAIR KERATIN AMINO ACIDS; SIMMONDSIA CHINENSIS SEED; WATER; CITRUS AURANTIFOLIA SEED OIL; CYMBOPOGON SCHOENANTHUS OIL; BITTER ORANGE OIL; WATER; CITRIC ACID ACETATE; ORYZA SATIVA WHOLE; EUCALYPTUS GLOBULUS LEAF; SODIUM BENZOATE; POTASSIUM SORBATE

GZE Rosemary Hair CareSet

ACTIVE INGREDIENT

Rosemary oil

INACTIVE INGREDIENT

GZE Rosemary Shampoo Bar：

BITTER ORANGE OIL

POTASSIUM SORBATE

ORYZA SATIVA WHOLE

COCAMIDOPROPYL BETAINE

EUCALYPTUS GLOBULUS LEAF

CITRIC ACID ACETATE
CYMBOPOGON SCHOENANTHUS OIL
LIME OIL
SODIUM BENZOATE
WATER

GZE Rosemary Hair Oil：

COCODIMONIUM HYDROXYPROPYL HYDROLYZED KERATIN (1000 MW)
ASCORBIC ACID
RETINYL PROPIONATE
ASCORBYL PALMITATE
PANTHENOL
TOCOPHEROL
WATER
MENTHA PIPERITA LEAF
METHICONE (20 CST)

GZE Rosemary Conditioner Bar：

COCONUT OIL
COCOABUTTER
PANTHENOL
TOCOPHEROL
PARFUMIDINE

GZE Black Sesame Rosemary Keratin Hair Mask：

JOJOBA OIL
HAIR KERATIN AMINO ACIDS
PANTHENOL
ASCORBYL TOCOPHERYL MALEATE
ASCORBIC ACID
FRAGRANCE 13576
DIMETHICONE
HYDROLYZED JOJOBA ESTERS (ACID FORM)
ETHYLHEXYLGLYCERIN
CETEARYL STEARATE
WATER

PURPOSE

GZE rosemary hair care set for Hair Growth Strong Roots Hair Strengthening for All Hair Types。

INDICATIONS AND USAGE

Step1: Wet your hair with warm water.

Step2: Take an appropriate amount of product and whip it into foam,apply it evenly onyour hair, and rub it to clean your scalp.

Step3: Add 10-12 drops of rosemary essential oil to shampoo to enhance hair care effect.

Step4: Clean the foam with warm water.Wash again with hair conditioner soap.Let your hair dry and apply a hair mask.

WARNINGS

For external use only.

Stop use and ask a doctor if rash occurs.

Do not use on damaged or broken skin.

When using this product keep out of eyes. Rinse with water to remove.

Keep out of reach of children. If swallowed, get medical help or contact a Poison Control Center right away.

DOSAGE AND ADMINISTRATION

Step1: Wet your hair with warm water.

Step2: Take an appropriate amount of product and whip it into foam,apply it evenly onyour hair, and rub it to clean your scalp.

Step3: Add 10-12 drops of rosemary essential oil to shampoo to enhance hair care effect.

Step4: Clean the foam with warm water.Wash again with hair conditioner soap.Let your hair dry and apply a hair mask.